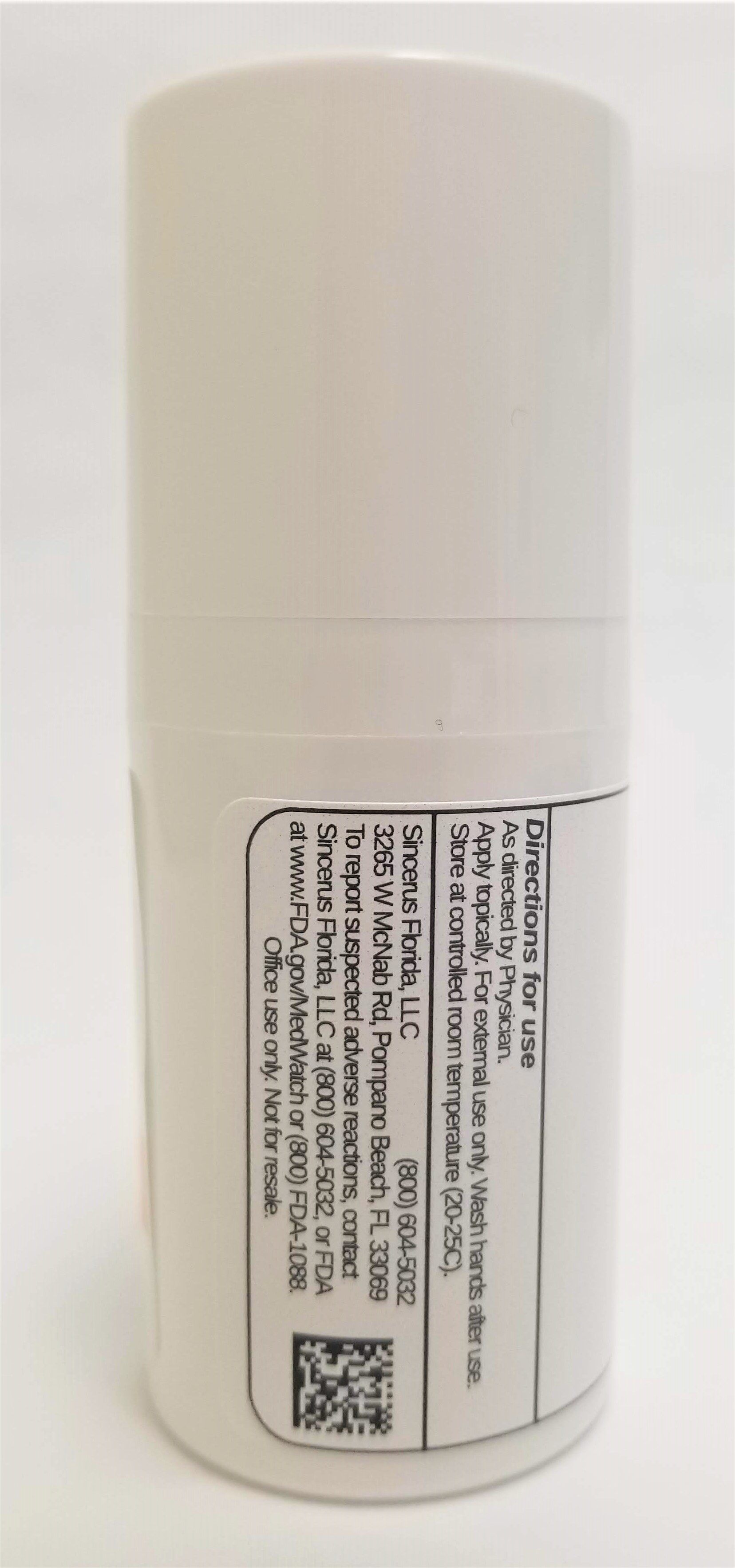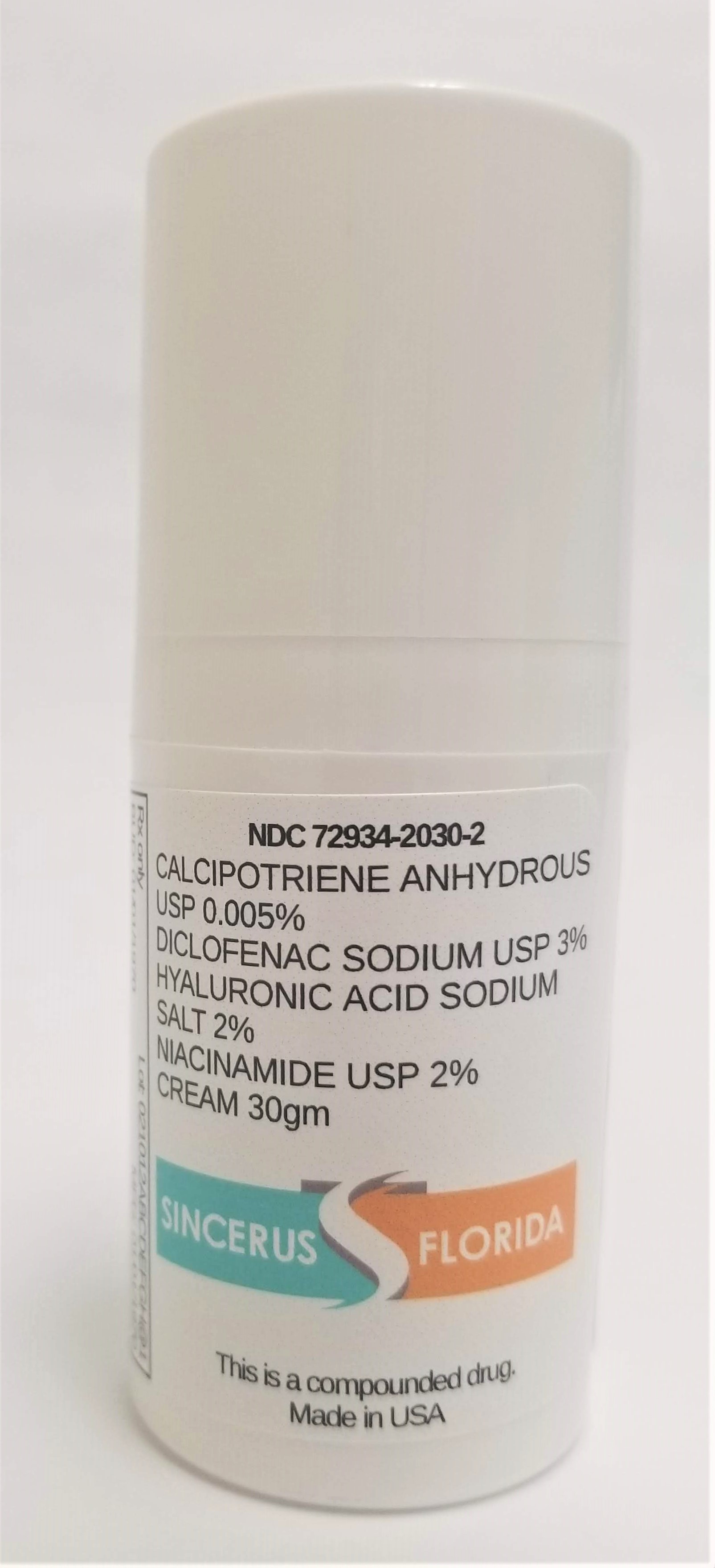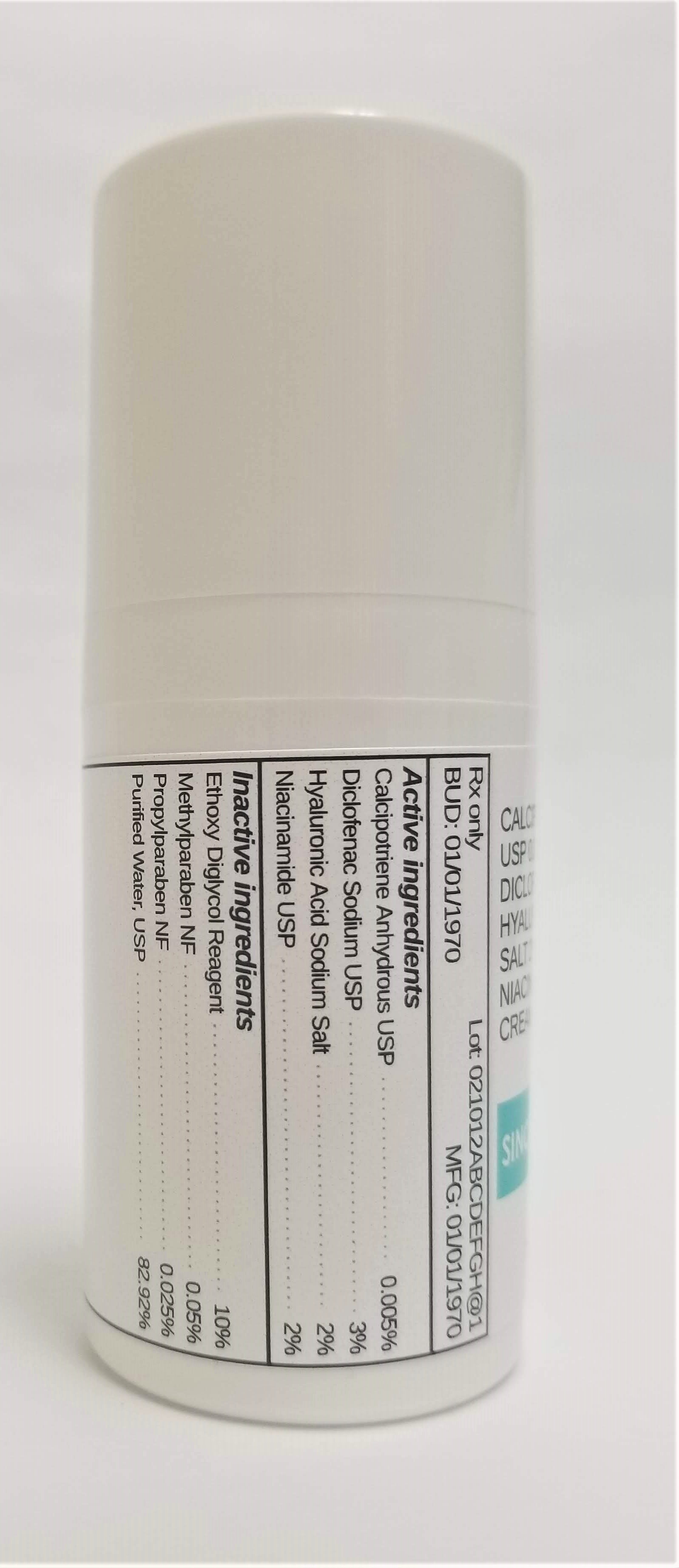 DRUG LABEL: CALCIPOTRIENE 0.005% / DICLOFENAC SODIUM 3% / HYALURONIC ACID SODIUM SALT 2% / NIACINAMIDE 2%
NDC: 72934-2030 | Form: CREAM
Manufacturer: Sincerus Florida, LLC
Category: prescription | Type: HUMAN PRESCRIPTION DRUG LABEL
Date: 20190506

ACTIVE INGREDIENTS: CALCIPOTRIENE 0.005 g/100 g; DICLOFENAC SODIUM 3 g/100 g; HYALURONATE SODIUM 2 g/100 g; NIACINAMIDE 2 g/100 g

CALCIPOTRIENE 0.005% / DICLOFENAC SODIUM 3% / HYALURONIC ACID SODIUM SALT 2% / NIACINAMIDE 2%